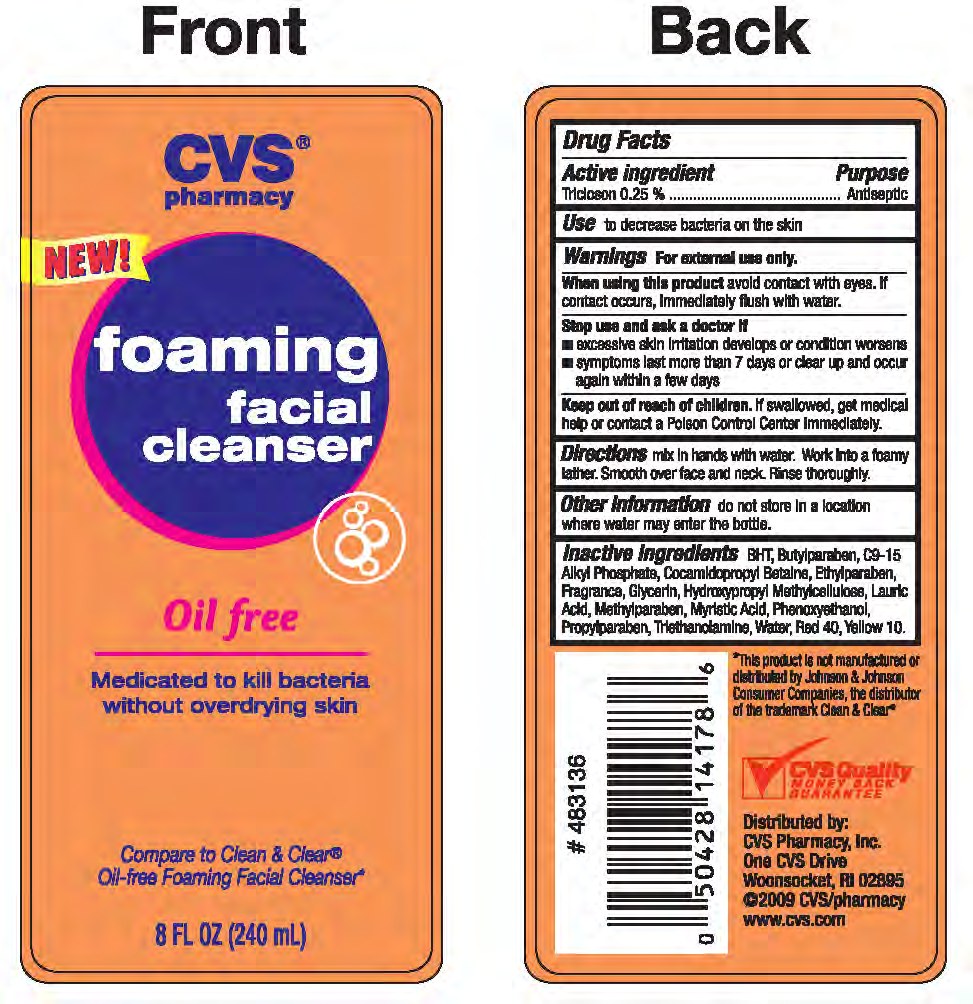 DRUG LABEL: TRICLOSAN
NDC: 59779-081 | Form: LIQUID
Manufacturer: CVS Pharmacy
Category: otc | Type: HUMAN OTC DRUG LABEL
Date: 20110216

ACTIVE INGREDIENTS: TRICLOSAN 29 mg/1 mL
INACTIVE INGREDIENTS: ISOPROPYL PALMITATE 712 mg/1 mL

drug facts

Active ingredient Purpose
Triclosan 0.25%...............................Antiseptic

Active ingredient Purpose
Triclosan 0.25%...............................Antiseptic
Use to decrease bacteria on the skin

Keep out of reach of children. If swallowed, get medical help
or contact a Poison Control Center Immediately.

INDICATIONS AND USAGE

Directions mix in hands with water. Work into a foamy lather.

Smooth over face and neck. Rinse thoroughly.

Warnings For external use only.
Stop use and ask a doctor if
- excessive skin irritation develops or condition worsens
- symptoms last more than 7 days or clear up and occur
again within a few days.
Keep out of reach of children. If swallowed, get medical
help or contact a Poison Control Center Immediately.

Directions
- Mix in hands with water. Work into a foamy lather.
Smooth over face and neck. Rinse thoroughly.
Other Information do not store in a location where water may enter the bottle

Inactive Ingredients BHT, Butylparaben, C9-15 Alkyl Phosphate,
Cocamidopropyl Bataine, Ethylparaben, Fragrance, Glycerin,
Hydroxypropyl Methylcelluose, Lauric Acid, Methylparaben, Myristic Acid,
Phenoxyethanol, Propylparaben, Triethanolamine, Water, Red 40, Yellow 10